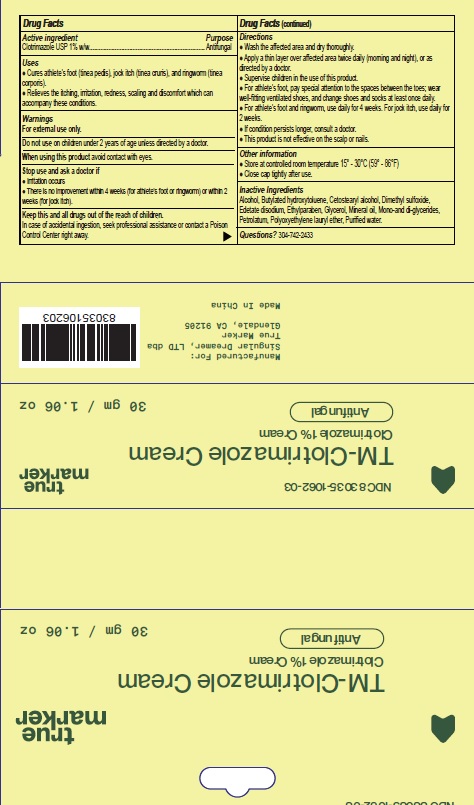 DRUG LABEL: TM-Clotrimazole
NDC: 83035-1062 | Form: CREAM
Manufacturer: Singular Dreamer, Ltd dba True Marker
Category: otc | Type: HUMAN OTC DRUG LABEL
Date: 20251006

ACTIVE INGREDIENTS: CLOTRIMAZOLE 1 g/100 g
INACTIVE INGREDIENTS: BUTYLATED HYDROXYTOLUENE; ALCOHOL; CETOSTEARYL ALCOHOL; DIMETHYL SULFOXIDE; EDETATE DISODIUM; ETHYLPARABEN; GLYCERIN; MINERAL OIL; GLYCERYL MONO AND DIPALMITOSTEARATE; PETROLATUM; GLYCERETH-31; WATER

Active ingredients

Clotrimazole USP 1% w/w

Purpose

Antifungal

Uses

- Cures athlete's foot (tinea pedis), jock itch (tinea cruris), and ringworm (tinea corporis).
- Relieves the itching, irritation, redness, scaling and discomfort which can accompany these conditions.

Warnings

- For external use only
- Do Not Use – On children under 2 years of age unless directed by a doctor.
- When using this product, avoid contact with eyes.
- Stop use and ask a doctor if
  ● Irritation occurs
  ● There is no improvement within 4 weeks (for athlete's foot or ringworm) or within 2 weeks (for jock itch).
- Keep out of reach of children. In case of accidental ingestion, seek professional assistance or contact a Poison Control Center right away.

Directions

- Wash the affected area and dry thoroughly.
- Apply a thin layer over affected area twice daily (morning and night), or as directed by a doctor.
- Supervise children in the use of this product.
- For athlete's foot, pay special attention to the spaces between the toes; wear well-fitting ventilated shoes, and change shoes and socks at least once daily.
- For athlete's foot and ringworm, use daily for 4 weeks. For jock itch, use daily for 2 weeks.
- If condition persists longer, consult a doctor.
- This product is not effective on the scalp or nails.

Other information

- Store at controlled room temperature 15° - 30°C (59° - 86°F)
- Close cap tightly after use.

Inactive ingredients

Alcohol, Butylated hydroxytoluene, Cetostearyl alcohol, Dimethyl sulfoxide, Edetate disodium, Ethylparaben, Glycerol, Mineral oil, Mono-and di-glycerides,Petrolatum, Polyoxyethylene lauryl ether, Purified water.

Questions?

304-742-2433